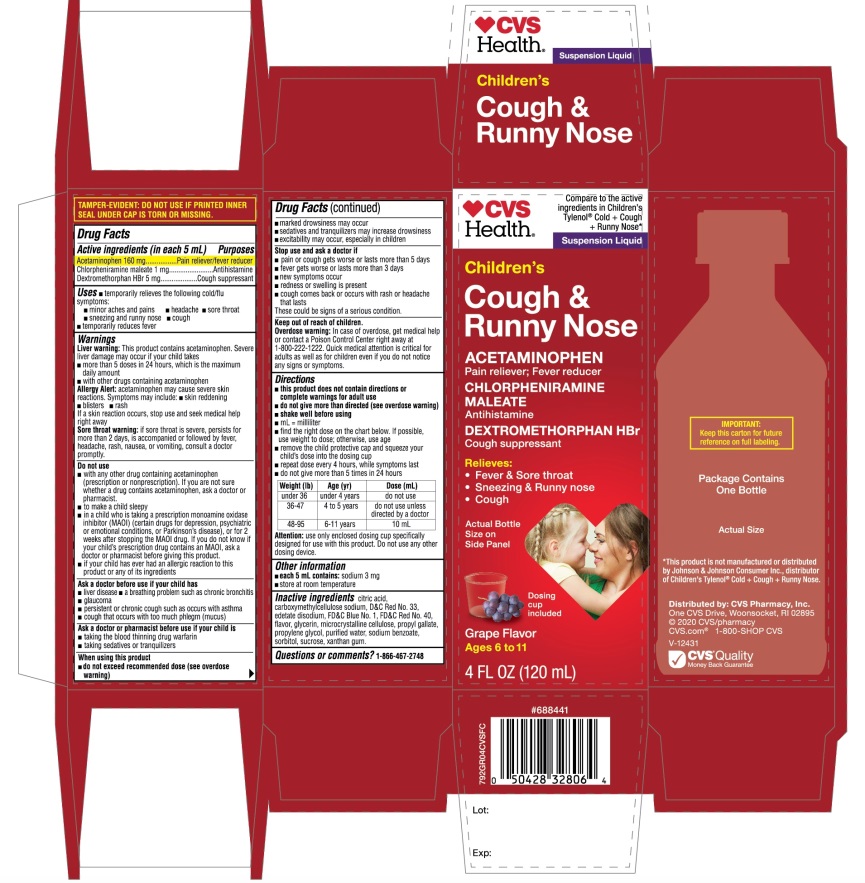 DRUG LABEL: CVS Childrens

NDC: 69842-792 | Form: SUSPENSION
Manufacturer: CVS
Category: otc | Type: HUMAN OTC DRUG LABEL
Date: 20251210

ACTIVE INGREDIENTS: ACETAMINOPHEN 160 mg/5 mL; CHLORPHENIRAMINE MALEATE 1 mg/5 mL; DEXTROMETHORPHAN HYDROBROMIDE 5 mg/5 mL
INACTIVE INGREDIENTS: ANHYDROUS CITRIC ACID; CARBOXYMETHYLCELLULOSE SODIUM, UNSPECIFIED; D&C RED NO. 33; EDETATE DISODIUM; FD&C BLUE NO. 1; FD&C RED NO. 40; GLYCERIN; MICROCRYSTALLINE CELLULOSE; PROPYL GALLATE; PROPYLENE GLYCOL; WATER; SODIUM BENZOATE; SORBITOL; SUCROSE; XANTHAN GUM

CVS Health Children's COLD + Cough & Runny Nose

Drug Facts

ACTIVE INGREDIENT

PURPOSE

Active ingredients (in each 5 mL) | Purposes
Acetaminophen 160 mg | Pain reliever/fever reducer
Chlorpheniramine maleate 1 mg | Antihistamine
Dextromethorphan HBr 5 mg | Cough suppressant

Uses

- temporarily relieves the following cold/flu symptoms:
  - minor aches and pains
  - headache
  - sore throat
  - sneezing and runny nose
  - cough
- temporarily reduces fever

Warnings

Liver warning:

This product contains acetaminophen. Severe liver damage may occur if your child takes

- more than 5 doses in 24 hours, which is the maximum daily amount
- with other drugs containing acetaminophen

Allergy alert:acetaminophen may cause severe skin reactions.

Symptoms may include:

- skin reddening
- blisters
- rash

If a skin reaction occurs, stop use and seek medical help right away.

Sore throat warning:if sore throat is severe, persists for more than 2 days, is accompanied or followed by fever, headache, rash, nausea, or vomiting, consult a doctor promptly.

Do not use

- with any other drug containing acetaminophen (prescription or nonprescription). If you are not sure whether a drug contains acetaminophen, ask a doctor or pharmacist.
- to make a child sleepy
- in a child who is taking a prescription monoamine oxidase inhibitor (MAOI) (certain drugs for depression, psychiatric or emotional conditions, or Parkinson's disease), or for 2 weeks after stopping the MAOI drug. If you do not know if your child's prescription drug contains an MAOI, ask a doctor or pharmacist before giving this product.
- if your child has ever had an allergic reaction to this product or any of its ingredients

Ask a doctor before use if your child has

- liver disease
- a breathing problem such as chronic bronchitis
- glaucoma
- persistent or chronic cough such as occurs with asthma
- cough that occurs with too much phlegm (mucus)

Ask a doctor or pharmacist before use if your child is

- taking the blood thinning drug warfarin
- taking sedatives or tranquilizers

When using this product

- do not exceed recommended dose (see overdose warning)
- marked drowsiness may occur
- sedatives and tranquilizers may increase drowsiness
- excitability may occur, especially in children

Stop use and ask a doctor if

- pain or cough gets worse or lasts more than 5 days
- fever gets worse or lasts more than 3 days
- new symptoms occur
- redness or swelling is present
- cough comes back or occurs with rash or headache that lasts

These could be signs of a serious condition.

Keep out of reach of children.

Overdose warning

In case of overdose, get medical help or contact a Poison Control Center right away. (1-800-222-1222) Quick medical attention is critical for adults as well as for children even if you do not notice any signs or symptoms.

Directions

- this product does not contain directions or complete warnings for adult use
- do not give more than directed (see overdose warning)
- shake well before using
- mL = milliliter
- find right dose on chart below. If possible, use weight to dose; otherwise, use age.
- remove the child protective cap and squeeze your child's dose into the dosing cup
- repeat dose every 4 hours, while symptoms last
- do not give more than 5 times in 24 hours

Weight (lb) | Age (yr) | Dose (mL)
under 36 | under 4 years | do not use
36-47 | 4 to 5 years | do not use unless directed by a doctor
48-95 | 6 to 11 years | 10 mL

Attention:use only enclosed dosing cup specifically designed for use with this product. Do not use any other dosing device.

Other information

- each 5 mL contains:sodium 3 mg
- store at room temperature

TAMPER-EVIDENT: DO NOT USE IF PRINTED INNER SEAL UNDER CAP IS TORN OR MISSING

Inactive ingredients

anhydrous citric acid, carboxymethylcellulose sodium, D&C Red No. 33, edetate disodium, FD&C Blue No. 1, FD&C Red No. 40, flavors, glycerin, microcrystalline cellulose, propyl gallate, propylene glycol, purified water, sodium benzoate, sorbitol solution, sucrose, xanthan gum

Questions or comments?

1-866-467-2748

PRINCIPAL DISPLAY PANEL

NDC 69842-792-04

CVS Health®

Compare to the active ingredients in Children’s Tylenol®Cold + Cough + Runny Nose*

Suspension Liquid

Children's Cough &
Runny Nose

ACETAMINOPHEN,

Pain Reliever-Fever Reducer

CHLORPHENIRAMINE MALEATE,

Antihistamine
DEXTROMETHORPHAN HBr

Cough Suppressant

Relieves:

- Fever & Sore Throat
- Sneezing & Runny Nose
- Cough

Dosing cup included

Grape Flavor

Ages 6-11

4 FL OZ (120 mL)

IMPORTANT: Keep this carton for future reference on full labeling.

Package contains One Bottle

Distributed by:

CVS Pharmacy, Inc.

One CVS Drive, Woonsocket, RI 02895

© 2020 CVS/pharmacy

CVS.com® 1-800-SHOP CVS

V-12431

CVS®Quality

Money Back Guarantee

*This product is not manufactured or distributed by Johnson & Johnson Consumer Inc., distributor of Children’s Tylenol®Cold + Cough + Runny Nose.